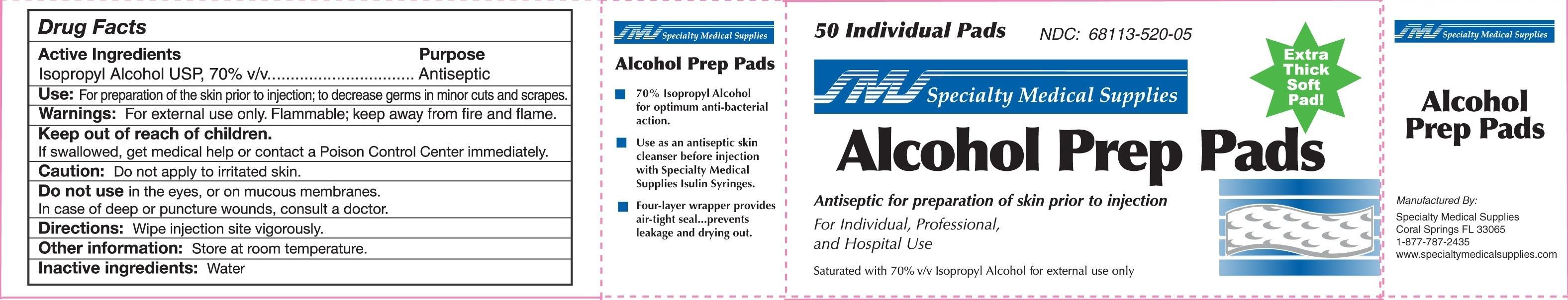 DRUG LABEL: Alcohol Prep
NDC: 68113-520 | Form: SWAB
Manufacturer: CARIBBEAN MEDICAL BROKERS, INC
Category: otc | Type: HUMAN OTC DRUG LABEL
Date: 20130419

ACTIVE INGREDIENTS: ISOPROPYL ALCOHOL 70 1/1 1
INACTIVE INGREDIENTS: WATER

Drug Facts

Active Ingredients

Isopropyl Alcohol USP, 70% v/v

Purpose

Antiseptic

Use

For preparation of the skin prior to injection; to decrease germs in minor cuts and scrapes.

Warnings:

For external use only. Flammable; keep away from fire and flame.

Keep out of reach of children.
If swallowed, get medical help or contact a Poison Control Center immediately.

Caution:

Do not apply to irritated skin.

Do not use in the eyes, or on mucous membranes.

In case of deep or puncture wounds, consult a doctor.

Directions:

Wipe injection site vigorously.

Other Information:

Store at room temperature.

Inactive ingredients:

Water

Principal Display Panel

50 Individual Pads
SMS Specialty Medical Supplies

Alcohol Prep Pads
Extra Thick Soft Pad!

Antiseptic for preparation of skin prior to injection

For Individual, Professional, and Hospital Use

Saturated with 70% v/v Isopropyl Alcohol for external use only